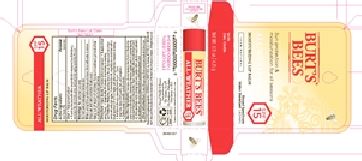 DRUG LABEL: ALL WEATHER SPF 15 LIP BALM
NDC: 26052-036 | Form: STICK
Manufacturer: Burt's Bees
Category: otc | Type: HUMAN OTC DRUG LABEL
Date: 20181217

ACTIVE INGREDIENTS: ZINC OXIDE 11 g/100 g
INACTIVE INGREDIENTS: COCOA BUTTER; ISOAMYL LAURATE; JOJOBA OIL; POLYHYDROXYSTEARIC ACID (2300 MW); OLIVE OIL; YELLOW WAX; CITRIC ACID MONOHYDRATE; JOJOBA OIL, RANDOMIZED; TOCOPHEROL; SOYBEAN OIL; SHEA BUTTER; ORANGE PEEL WAX; MEADOWFOAM SEED OIL; REBAUDIOSIDE A

Burt's Bees All Weather SPF 15 Lip Balm

ACTIVE INGREDIENTS

ZINC OXIDE 11%

PURPOSE

Sunscreen

Uses

Helps prevent sunburn.

If used as directed with other sun protection measures (see Directions), decreases the risk of skin cancer and early skin aging caused by the sun.

Warnings:

For external use only

Do not use on damaged or broken skin.

When using this product keep out of reach of eyes. Rinse with water to remove.

Stop use and ask a doctor if rash occurs.

Keep out of reach of children. If product is swallowed, get medical help or contact Poison Control Center right away.

Directions

Apply liberally 15 minutes before sun exposure.

Reapply at least every 2 hours.

Reappy after 40 minutes of swimming or weating.

Sun Protection Measures.

Spending time in the sun increases your risk of skin cancer and early skin aging. To decrease this risk, regularly use a sunscreen with a broad spectrum SPF of 15 or higher and other sun protection measuresincluding:

limit time in the sun, especially from 10 a.m. - 2 p.m.

wear long sleeve shirts, pants, hats and sunglasses.

Children under 6 months consult a doctor.

Inactive Ingredients:

beeswax, olea europaea (olive) fruit oil, theobroma cacao (cocoa) seed butter, simmondsia chinensis (jojoba) seed oil, isoamyl laurate, butyrospermum parkii (shea) butter, flavor, limnanthes alba (meadowfoam) seed oil, citrus aurantium dulcis (orange) peel wax, jojoba esters, glycine soja (soybean) oil, tocopherol, citric acid, rebaudioside A, polyhydroxystearic acid

Other Information:

Protect this product from excessive heat and direct sun.

PACKAGE LABEL

BURTS BEES

ALL WEATHER SPF 15

MOISTURIZING LIP BALM